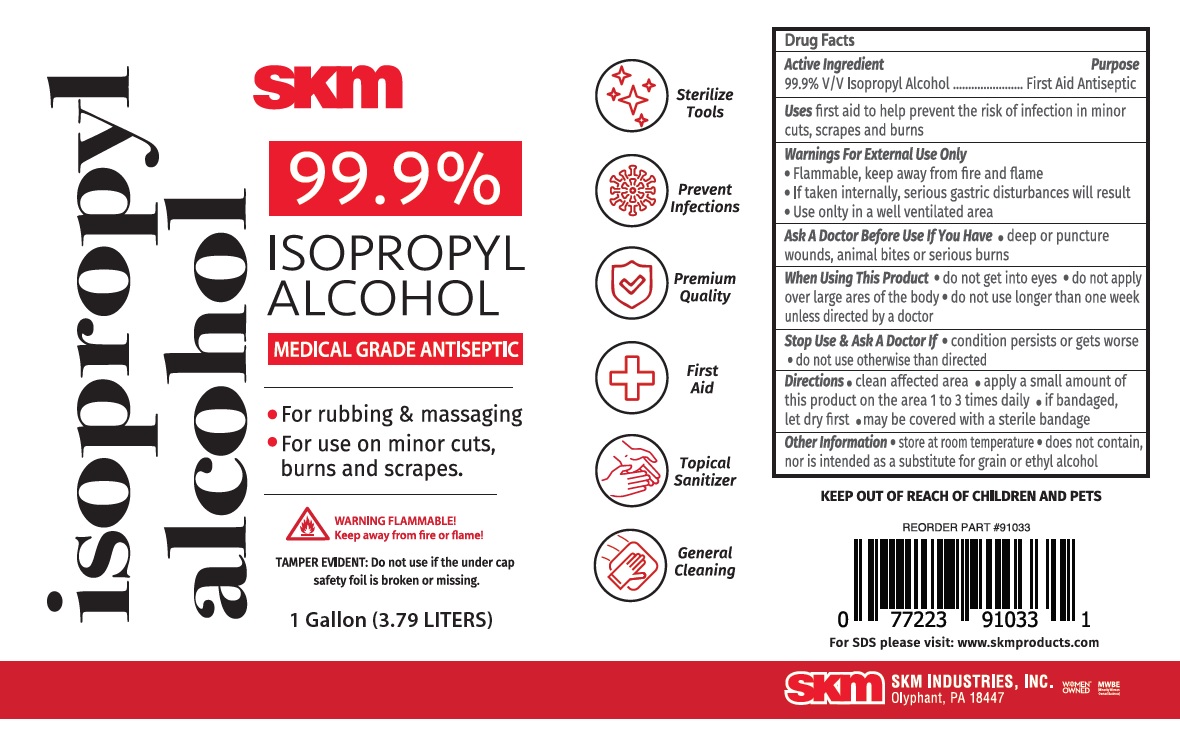 DRUG LABEL: SKM 99.9% ISOPROPYL ALCOHOL
NDC: 74990-990 | Form: LIQUID
Manufacturer: Skm Industries Inc.
Category: otc | Type: HUMAN OTC DRUG LABEL
Date: 20210108

ACTIVE INGREDIENTS: ISOPROPYL ALCOHOL 99.9 mL/100 mL
INACTIVE INGREDIENTS: WATER

SKM 99.9% ISOPROPYL ALCOHOL

Active Ingredient

99.9% V/V Isopropyl Alcohol

Purpose

First Aid Antiseptic

Uses

first aid to help prevent the risk of infection in minor cuts, scrapes and burns

Warnings For External Use Only

• Flammable, keep away from fire and flame
• If taken internally, serious gastric disturbances will result
• Use only in a well ventilated area

Ask A Doctor Before Use If You Have • deep or puncture wounds, animal bites or serious burns

When Using This Product • do not get into eyes • do not apply over large areas of the body • do not use longer than one week unless directed by a doctor

Stop Use & Ask A Doctor If • condition persists or gets worse • do not use otherwise than directed

KEEP OUT OF REACH OF CHILDREN AND PETS

Directions

• clean affected area • apply a small amount of this product on the area 1 to 3 times daily • if bandaged, let dry first • may be covered with a sterile bandage

Other Information

• store at room temperature • does not contain, nor is intended as a substitute for grain or ethyl alcohol

Inactive Ingredient

Water

MEDICAL GRADE ANTISEPTIC

• For rubbing & massaging
• For use on minor cuts, burns and scrapes.

WARNING FLAMMABLE!
Keep away from fire or flame!

TAMPER EVIDENT: Do not use if the under cap safety foil is broken or missing.

Sterilize Tools

Prevent Infections

Premium Quality

First Aid

Topical Sanitizer

General Cleaning

For SDS please visit: www.skmproducts.com

SKM INDUSTRIES, INC.

Olyphant, PA 18447

WOMEN OWNED

MWBE (Minority Women Owned Business)